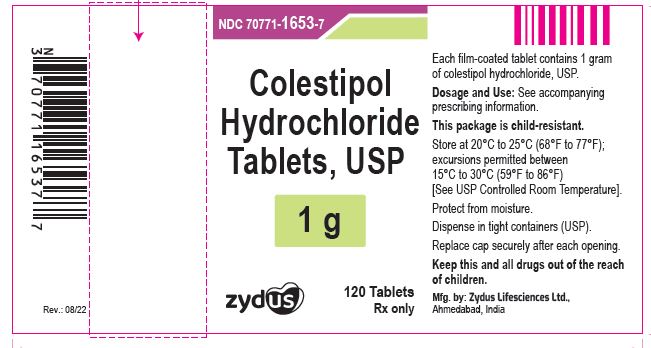 DRUG LABEL: Colestipol hydrochloride
NDC: 70771-1653 | Form: TABLET, FILM COATED
Manufacturer: Zydus Lifesciences Limited
Category: prescription | Type: HUMAN PRESCRIPTION DRUG LABEL
Date: 20241126

ACTIVE INGREDIENTS: COLESTIPOL HYDROCHLORIDE 1 g/1 1
INACTIVE INGREDIENTS: CELLACEFATE; CELLULOSE, MICROCRYSTALLINE; CROSPOVIDONE, UNSPECIFIED; FERRIC OXIDE YELLOW; HYPROMELLOSES; MAGNESIUM STEARATE; POLYVINYL ALCOHOL, UNSPECIFIED; POVIDONE, UNSPECIFIED; SILICON DIOXIDE; TRIACETIN

Colestipol Hydrochloride Tablets, USP

PACKAGE LABEL.PRINCIPAL DISPLAY PANEL

Colestipol hydrochloride tablets, 1 g

120 tablets

NDC 70771-1653-7

Rx only